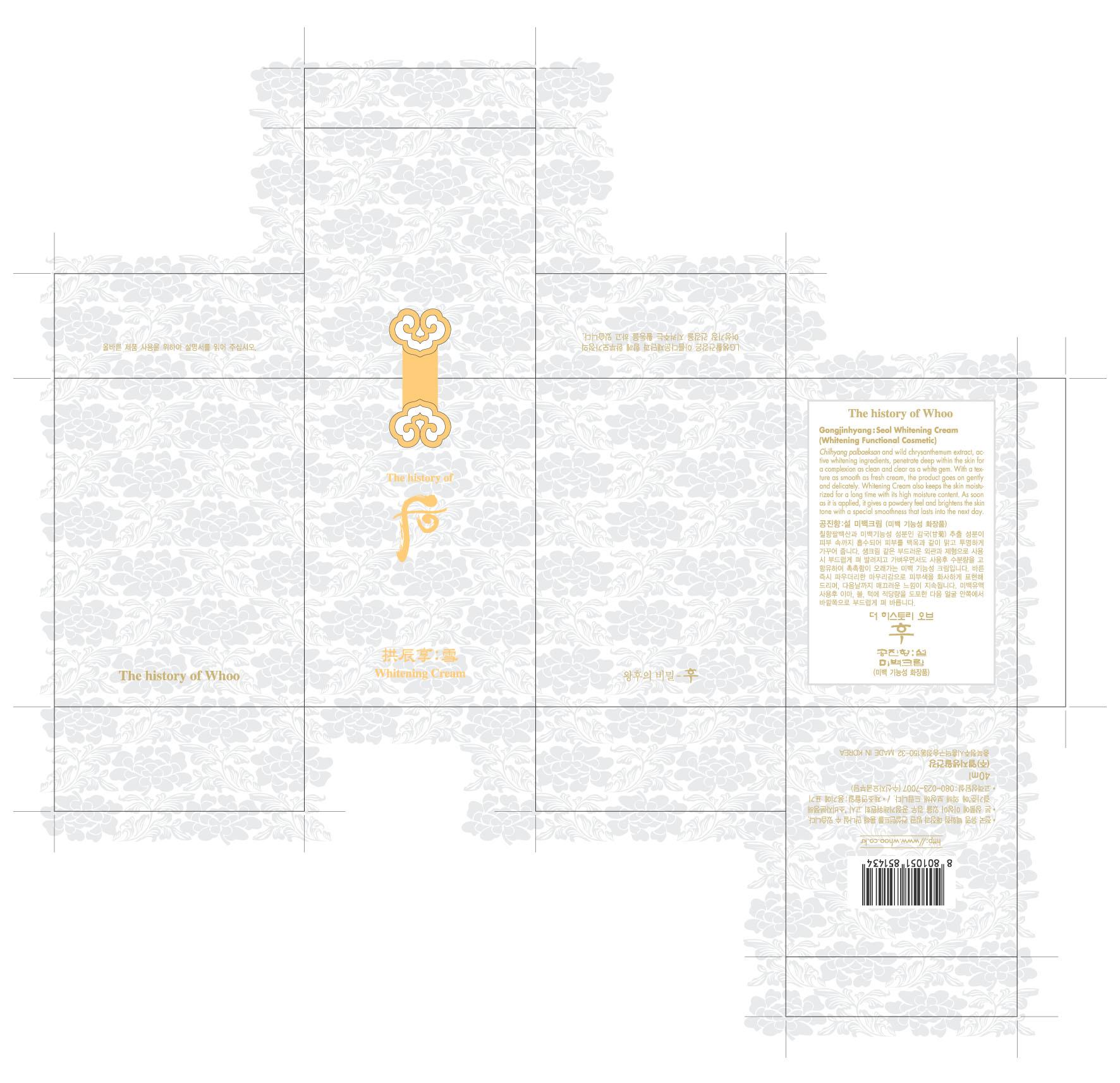 DRUG LABEL: GONGJINHYANG  SEOL WHITENING 
NDC: 53208-372 | Form: CREAM
Manufacturer: LG Household and Healthcare, Inc.
Category: otc | Type: HUMAN OTC DRUG LABEL
Date: 20100324

ACTIVE INGREDIENTS: DIOSMETIN 0.10 g/100 g
INACTIVE INGREDIENTS: CYCLOMETHICONE 5; DIPROPYLENE GLYCOL; BUTYLENE GLYCOL; GLYCERIN; ALUMINUM OXIDE; PANTHENOL; BETAINE; FILIPENDULA ULMARIA ROOT; METHYLPARABEN; ETHYLPARABEN

The History of Whoo Whitening Seol Cream

ACTIVE INGREDIENT

DIOSMETIN 0.10 g/100g

WARNINGS AND PRECAUTIONS

For external use only

Keep out of reach of children. Is swallowed, get medical help or contact a Poison Control Center right away.

WHEN USING

Keep out of eyes. Rinse with water to remove.

Stop use if a rash or irritation develops and lasts.